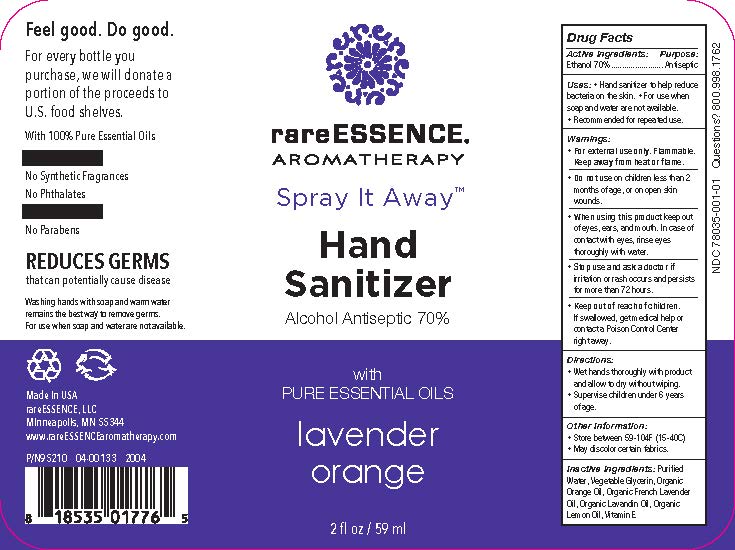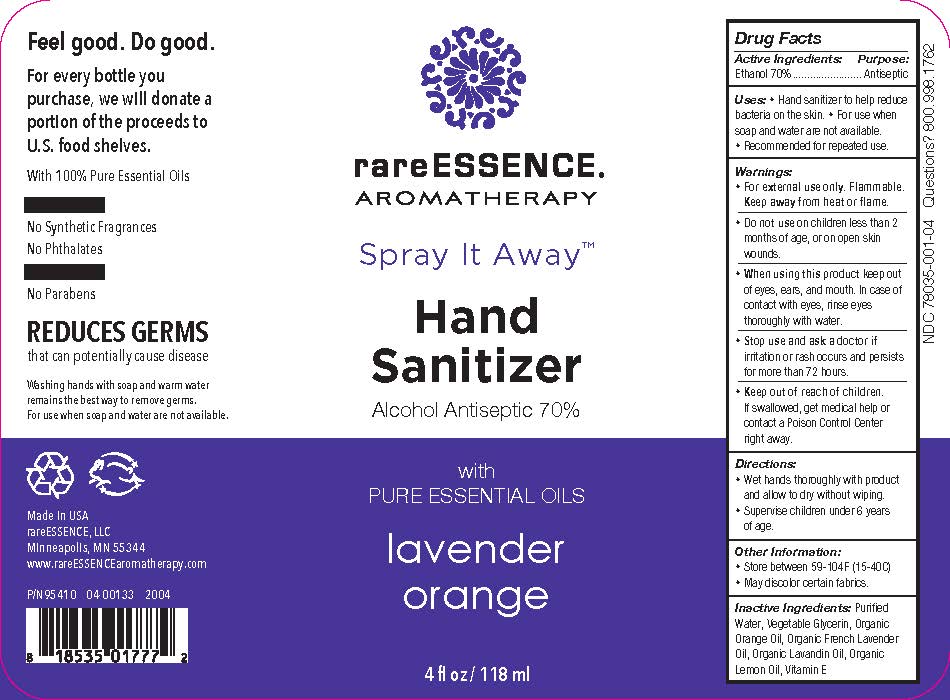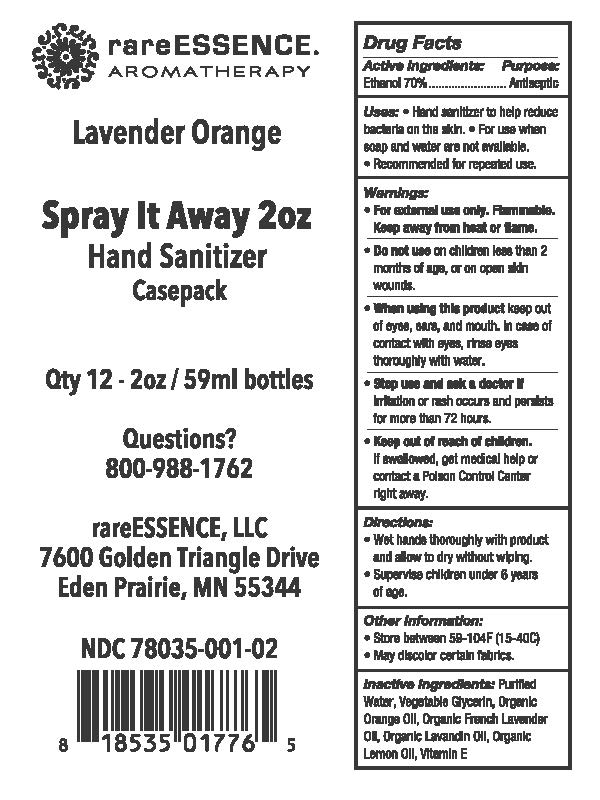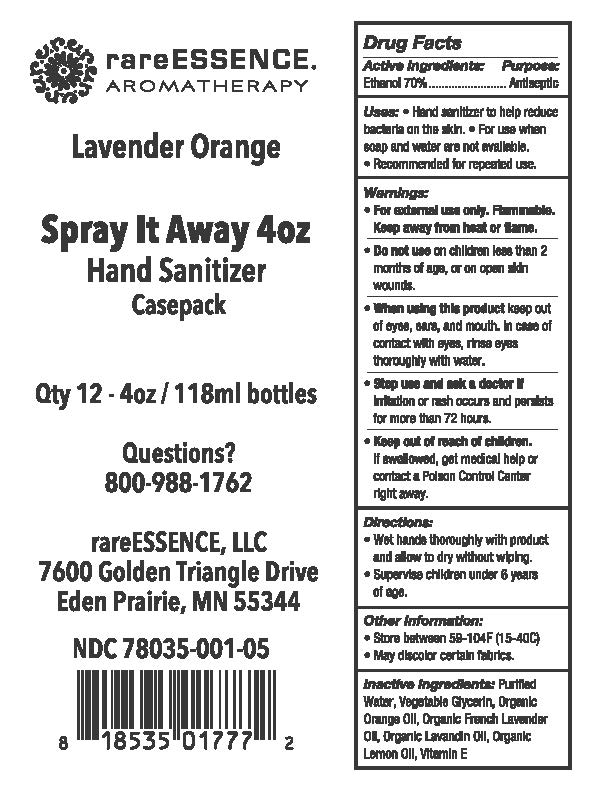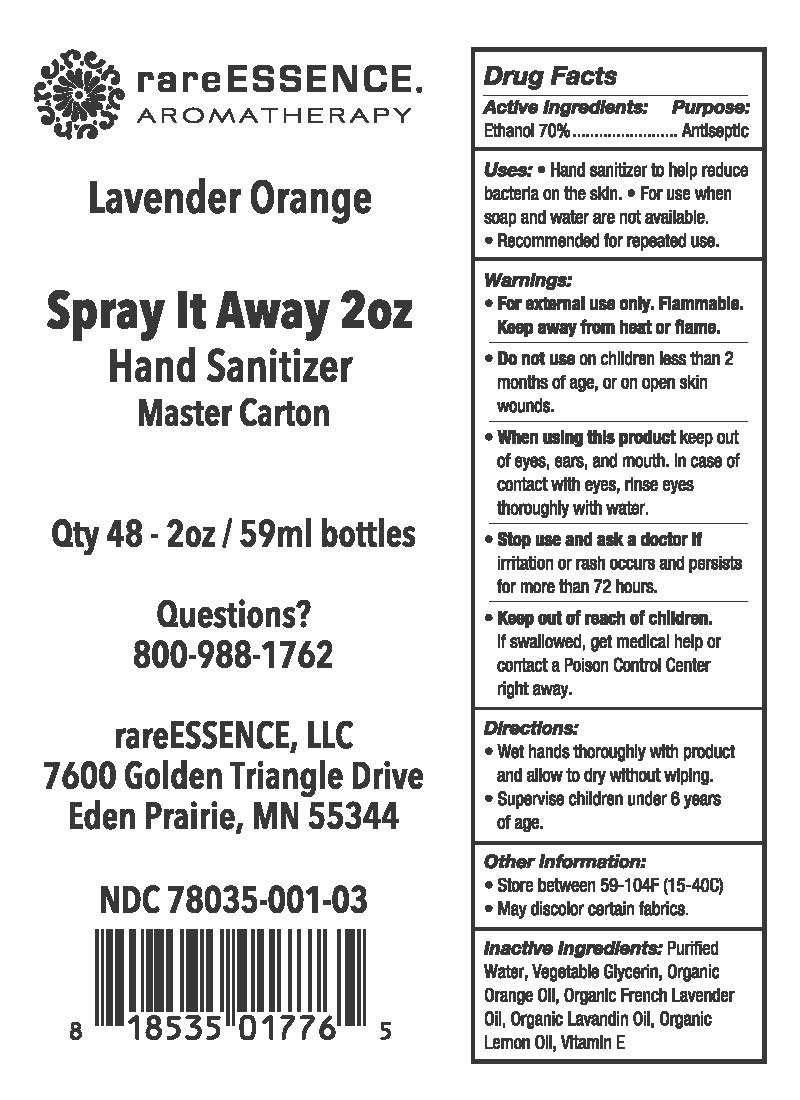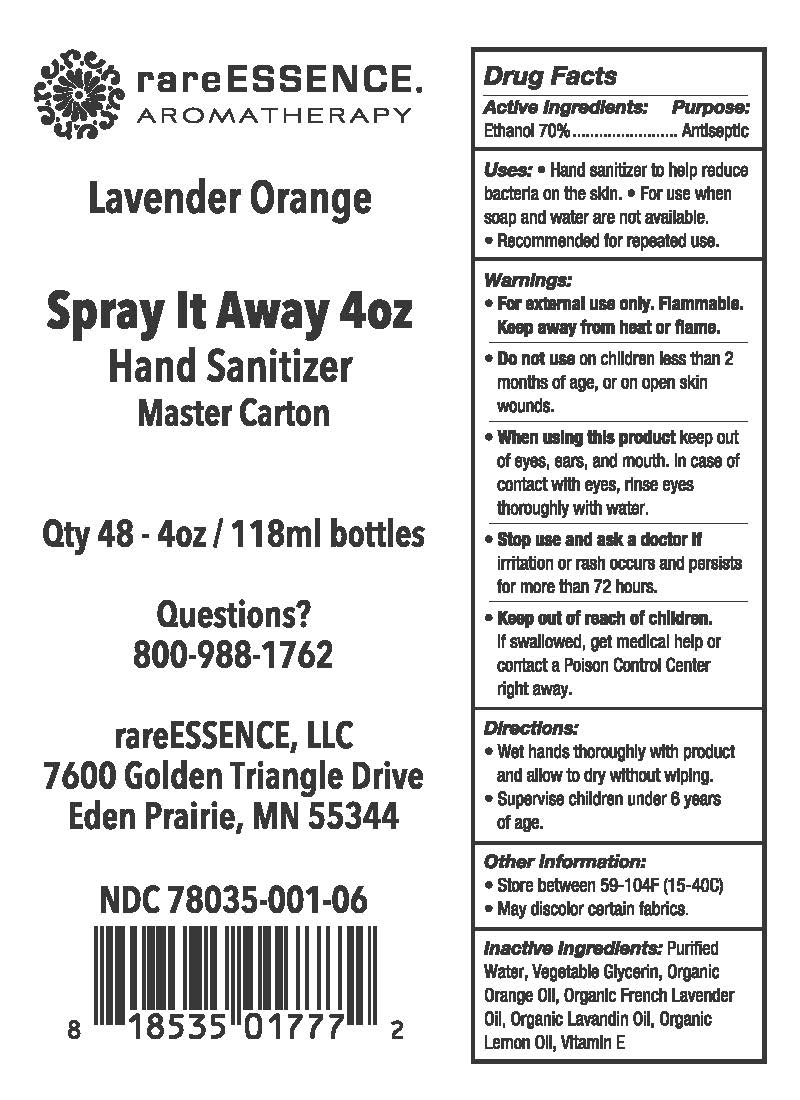 DRUG LABEL: rareESSENCE Hand Sanitizer
NDC: 78035-001 | Form: LIQUID
Manufacturer: rareESSENCE, LLC
Category: otc | Type: HUMAN OTC DRUG LABEL
Date: 20200602

ACTIVE INGREDIENTS: ALCOHOL 70 mL/100 mL
INACTIVE INGREDIENTS: WATER; ORANGE OIL; LAVENDER OIL; ALPHA-TOCOPHEROL; GLYCERIN; LEMON OIL

Drug Facts

ACTIVE INGREDIENT

Ethyl Alcohol 70%

PURPOSE

Hand & Skin Antiseptic

INDICATIONS AND USAGE

Hand & Skin Antiseptic to help decrease pathogens (germs) on the skin

WARNINGS

For external use only

Flammable: Keep away from heat and flame

WHEN USING

* Keep out of eyes, ears, and mouth.

* In case of contact with eyes, rinse eyes thoroughly with water.

ASK DOCTOR

* If irritation or rash occurs and persists for more than 72 hours.

STOP USE

* If irritation or rash occurs and persists for more than 72 hours.

KEEP OUT OF REACH OF CHILDREN

* If swallowed, get medical help or contact a Poison Control Center right away.

DOSAGE AND ADMINISTRATION

* Wet hands thoroughly with product and allow to dry without wiping.

* Supervise children under 6 years of age.

INACTIVE INGREDIENT

Purified water, Vegetable Glycerin, Organic orange oil, Organic French Lavender oil, Organic Lavandin oil, Organic Lemon Oil, Vitamin E

Questions? 800.998.1762

PACKAGE LABEL

rareESSENCE AROMATHERAPY

Spray It Away (TM)

Hand Sanitizer

Alcohol Antiseptic 70%

With Pure essential oils

Lavender orange

Feel good. Do good.

For every bottle you purchase, we will donate a portion of the proceeds to U.S. food shelves.

With 100% Pure Essential Oils

No Synthetic Frangrances

No Phthalates

No Parabens

Reduceds Germs that can potentially cause disease

Washing hands with soap and warm water remains the best way to remove germs. For use when souap and water are not available.

Made in USA

rareEssence, LLC

Minneapolis, MN 55344

www.rareEssenccearomatherapy.com

xx oz (zzzmL) NDC 78035-001-xx